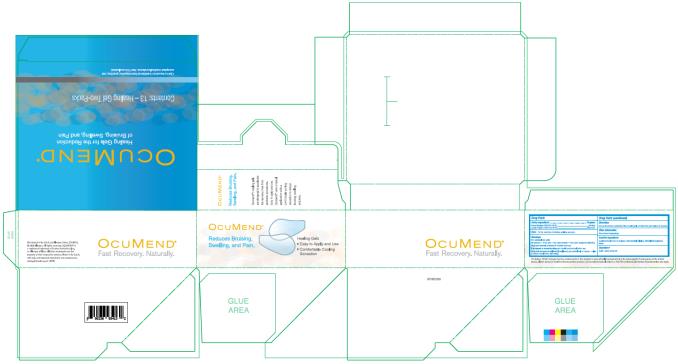 DRUG LABEL: OcuMend
NDC: 0023-6934 | Form: PATCH
Manufacturer: Allergan, Inc.
Category: homeopathic | Type: HUMAN OTC DRUG LABEL
Date: 20200617

ACTIVE INGREDIENTS: ARNICA MONTANA 50 [hp_X]/1 1; LEDUM PALUSTRE TWIG 50 [hp_X]/1 1
INACTIVE INGREDIENTS: HYDROXYETHYL CELLULOSE, UNSPECIFIED; METHYL DIETHANOLAMINE; WATER

Ocumend

ACTIVE INGREDIENTS

Arnica Montana 50M 50% HPUS

Ledum Palustre 50M 50% HPUS

HOMEOPATHIC PURPOSE

Arnica Montana 50M HPUS: Bruising

Ledum Palustre 50M HPUS: Black Eye

USES

For the reduction of bruising, swelling, and pain.

WARNINGS

For external use only

Do not use

in the eyes, over open wounds, or if you have unexpected bleeding

Stop use and ask a doctor if

condition worsens.

If pregnant or breast-feeding,

ask a health professional before use.

Keep out of reach of children.

If swallowed, get medical help or contact a Poison Control Center right away.

DIRECTIONS

Use as directed by a physician. Place healing gels on intact skin and replace as needed.

OTHER INFORMATION

Store at room temperature.

INACTIVE INGREDIENTS

Acrylates/Acrylamide Co-polymer, Hydroxyethyl Cellulose, Methyldiethanolamine, Water

QUESTIONS?

Call: 1 (800) 678-1605

DESCRIPTION:

The letters ‘HPUS’ indicate that the component(s) in this product is (are) officially monographed in the Homeopathic Pharmacopeia of the United States. Claims based on traditional homeopathic practice, not accepted medical evidence. Not FDA evaluated.

Do not use if peel pouches are open.

Principal Display Panel

OCUMEND®
Healing Gels for the Reduction
of Bruising, Swelling, and Pain
Contents: 13 – Healing Gel Two-Packs